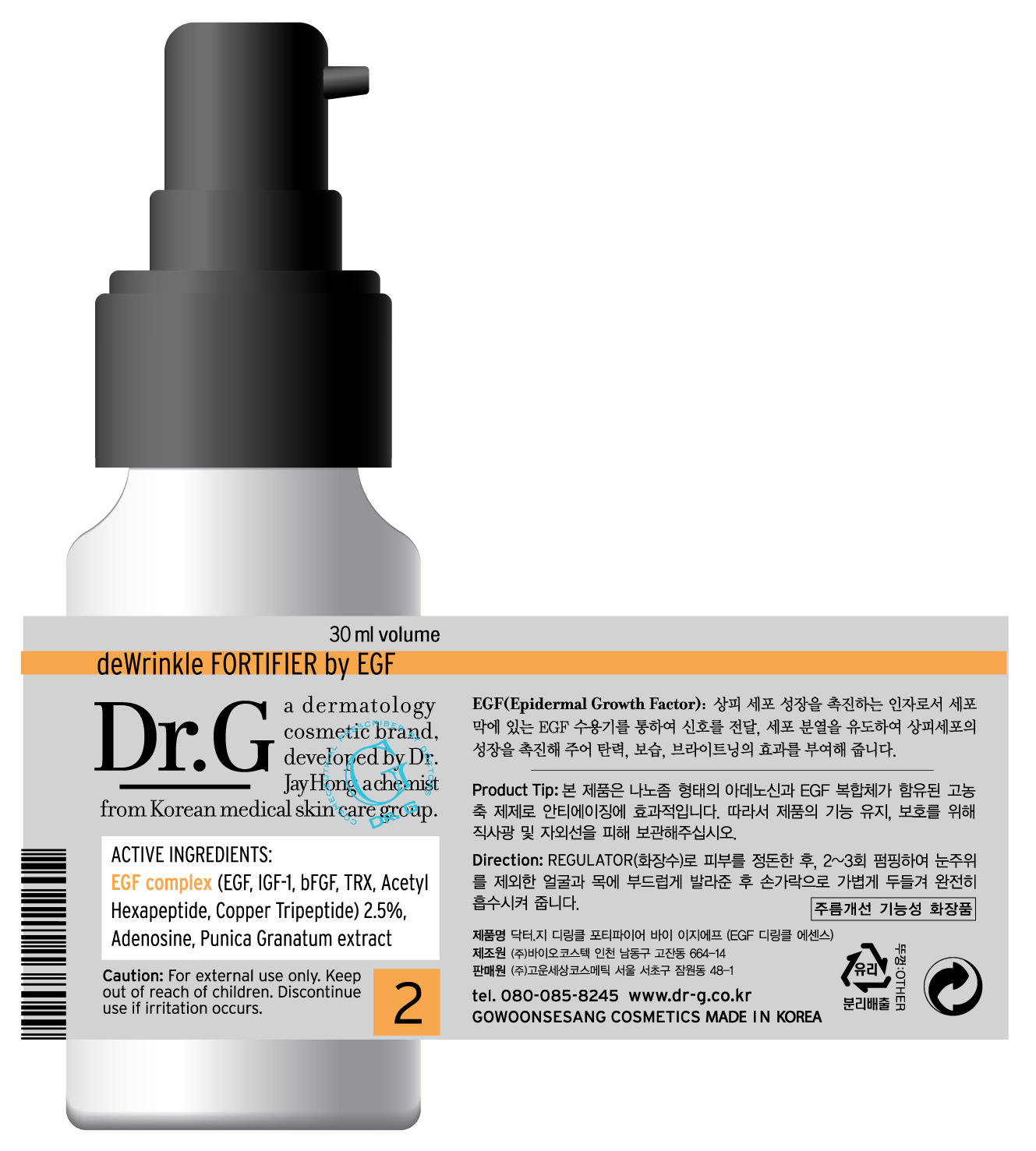 DRUG LABEL: Dr G deWrinkle FORTIFIER by EGF
NDC: 43948-3002 | Form: CREAM
Manufacturer: The Doctor's Cosmetic Inc
Category: otc | Type: HUMAN OTC DRUG LABEL
Date: 20091001

ACTIVE INGREDIENTS: ADENOSINE 0.012 mL/30 mL; GLYCERIN 2.1 mL/30 mL

ACTIVE INGREDIENTS:

Glycerin, EGF complex (EGF, IGF-1, bFGF, TRX, Acetyl Hexapeptide, Copper Tripeptide) 2.5%, Adenosine, Punica Granatum extract

KEEP OUT OF REACH OF CHILDREN

Caution: For external use only. Keep out of reach of children. Discontinue use if irritation occurs.

WHEN USING

DIRECTION OF USE: After conditioning skin with Regulator(toner) pump the essence 2 to 3 times and smoothly spread on face and neck.

PACKAGE LABEL

Label8c